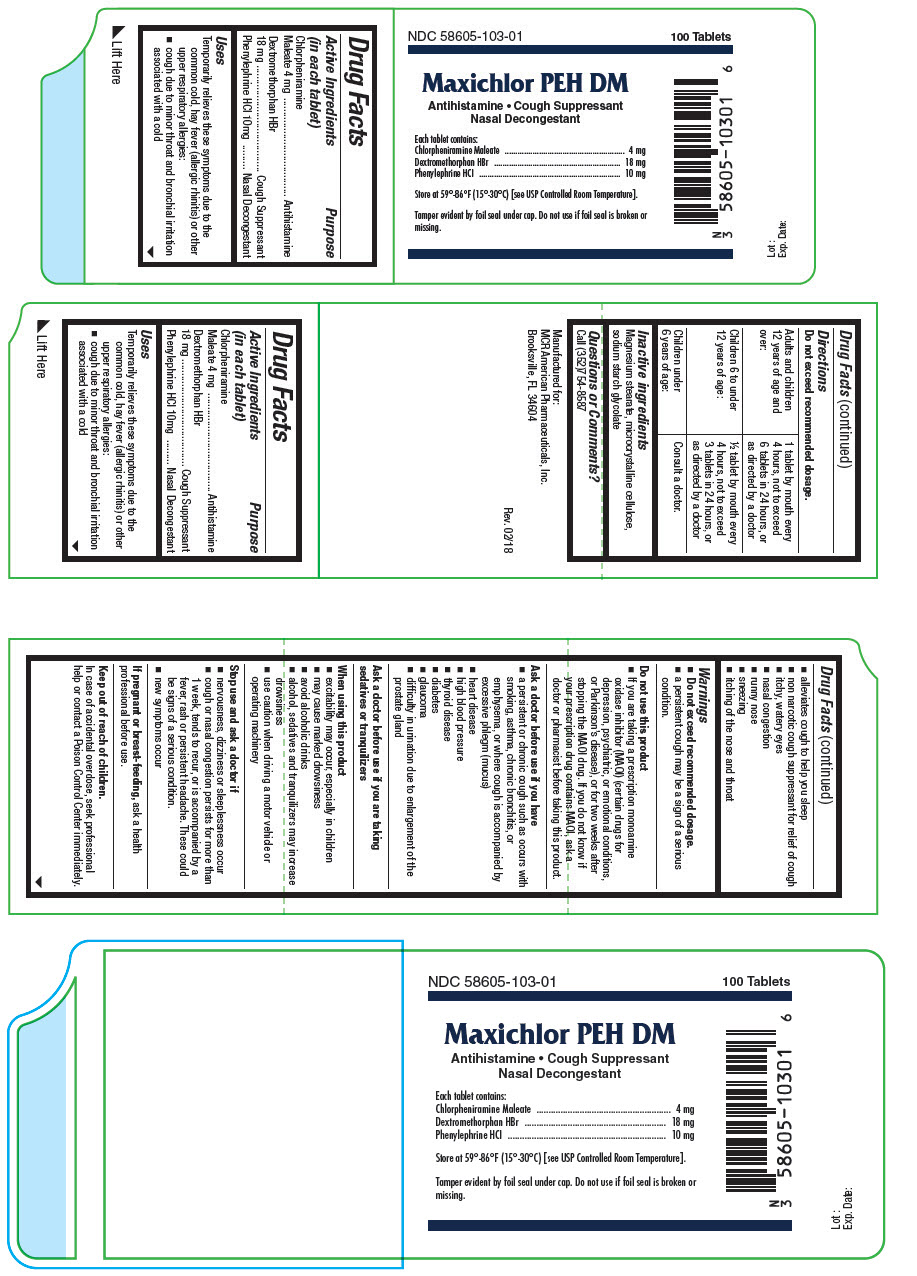 DRUG LABEL: Maxichlor PEH DM
NDC: 58605-103 | Form: TABLET
Manufacturer: MCR American Pharmaceuticals, Inc.
Category: otc | Type: HUMAN OTC DRUG LABEL
Date: 20180315

ACTIVE INGREDIENTS: CHLORPHENIRAMINE MALEATE 4 mg/1 1; DEXTROMETHORPHAN HYDROBROMIDE 18 mg/1 1; PHENYLEPHRINE HYDROCHLORIDE 10 mg/1 1
INACTIVE INGREDIENTS: Magnesium Stearate; Microcrystalline Cellulose; Sodium Starch Glycolate Type A Potato

Maxichlor PEH DM

Drug Facts

ACTIVE INGREDIENT

Active Ingredients (in each tablet) | Purpose
Chlorpheniramine Maleate 4 mg | Antihistamine
Dextromethorphan HBr 18 mg | Cough Suppressant
Phenylephrine HCl 10mg | Nasal Decongestant

Uses

Temporarily relieves these symptoms due to the common cold, hay fever (allergic rhinitis) or other upper respiratory allergies:

- cough due to minor throat and bronchial irritation associated with a cold
- alleviates cough to help you sleep
- non narcotic cough suppressant for relief of cough
- itchy, watery eyes
- nasal congestion
- runny nose
- sneezing
- itching of the nose and throat

Warnings

- Do not exceed recommended dosage.
- a persistent cough may be a sign of a serious condition.

Do not use this product

- If you are taking a prescription monoamine oxidase inhibitor (MAOI) (certain drugs for depression, psychiatric, or emotional conditions, or Parkinson's disease), or for two weeks after stopping the MAOI drug. If you do not know if your prescription drug contains MAOI, ask a doctor or pharmacist before taking this product.

Ask a doctor before use if you have

- a persistent or chronic cough such as occurs with smoking, asthma, chronic bronchitis, or emphysema, or where cough is accompanied by excessive phlegm (mucus)
- heart disease
- high blood pressure
- thyroid disease
- diabetes
- glaucoma
- difficulty in urination due to enlargement of the prostate gland

Ask a doctor before use if you are taking sedatives or tranquilizers

When using this product

- excitability may occur, especially in children
- may cause marked drowsiness
- avoid alcoholic drinks
- alcohol, sedatives and tranquilizers may increase drowsiness
- use caution when driving a motor vehicle or operating machinery

Stop use and ask a doctor if

- nervousness, dizziness or sleeplessness occur
- cough or nasal congestion persists for more than 1 week, tends to recur, or is accompanied by a fever, rash or persistent headache. These could be signs of a serious condition.
- new symptoms occur

PREGNANCY OR BREAST FEEDING

If pregnant or breast-feeding, ask a health professional before use.

Keep out of reach of children.

In case of accidental overdose, seek professional help or contact a Poison Control Center immediately.

Directions

Do not exceed recommended dosage.

Adults and children 12 years of age and over: | 1 tablet by mouth every 4 hours, not to exceed 6 tablets in 24 hours, or as directed by a doctor
Children 6 to under 12 years of age: | ½ tablet by mouth every 4 hours, not to exceed 3 tablets in 24 hours, or as directed by a doctor
Children under 6 years of age: | Consult a doctor.

Inactive ingredients

Magnesium stearate, microcrystalline cellulose, sodium starch glycolate

Questions or Comments?

Call (352)754-8587

PRINCIPAL DISPLAY PANEL - 4 mg/18 mg/10 mg Tablet Bottle Label

NDC 58605-103-01
100 Tablets

Maxichlor PEH DM

Antihistamine • Cough Suppressant
Nasal Decongestant

Each tablet contains:
Chlorpheniramine Maleate 4 mg
Dextromethorphan HBr 18 mg
Phenylephrine HCl 10 mg

Store at 59°-86°F (15°-30°C) [see USP Controlled Room Temperature].

Tamper evident by foil seal under cap. Do not use if foil seal is broken or
missing.